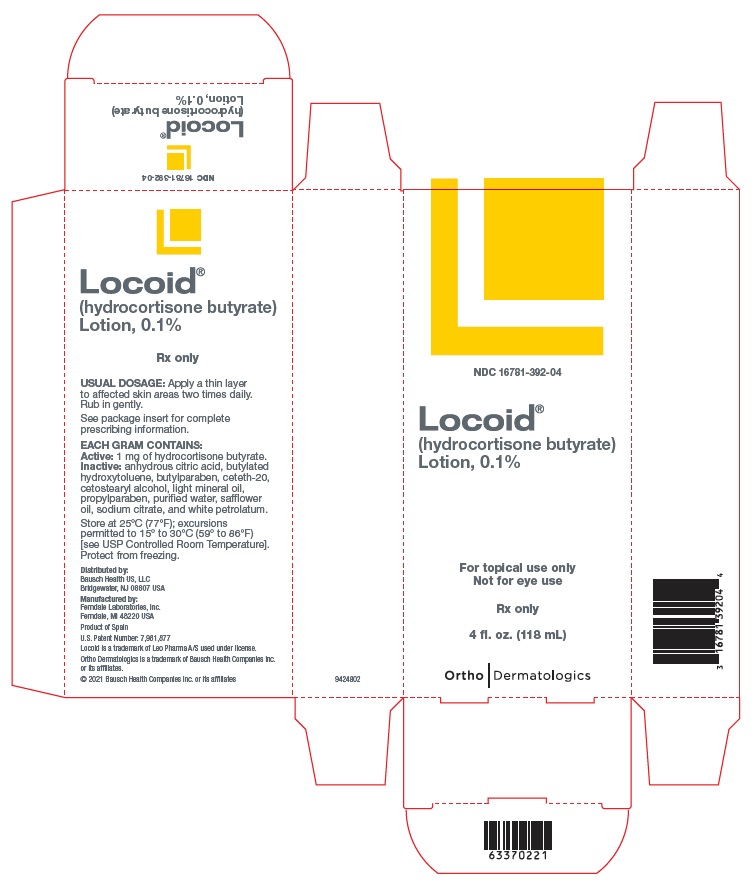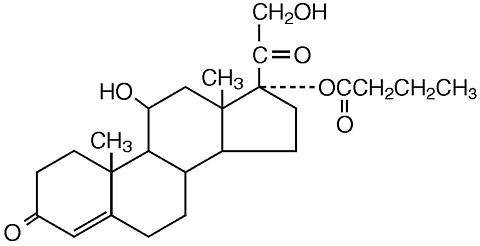 DRUG LABEL: Locoid
NDC: 16781-392 | Form: LOTION
Manufacturer: Bausch Health US, LLC
Category: prescription | Type: HUMAN PRESCRIPTION DRUG LABEL
Date: 20231030

ACTIVE INGREDIENTS: HYDROCORTISONE BUTYRATE 1 mg/1 mL
INACTIVE INGREDIENTS: ANHYDROUS CITRIC ACID; CETETH-20; CETOSTEARYL ALCOHOL; BUTYLATED HYDROXYTOLUENE; BUTYLPARABEN; LIGHT MINERAL OIL; PROPYLPARABEN; WATER; SAFFLOWER OIL; SODIUM CITRATE, UNSPECIFIED FORM; PETROLATUM

HIGHLIGHTS OF PRESCRIBING INFORMATION

These highlights do not include all the information needed to use LOCOID Lotion safely and effectively. See full prescribing information for LOCOID Lotion.
LOCOID® (hydrocortisone butyrate) lotion, for topical use
Initial U.S. Approval: 1982

1 INDICATIONS AND USAGE

LOCOID Lotion is a corticosteroid indicated for the topical treatment of mild to moderate atopic dermatitis in patients 3 months of age and older. (1)

2 DOSAGE AND ADMINISTRATION

- Apply a thin layer to the affected skin two times daily. (2)
- Rub in gently. (2)
- Discontinue LOCOID Lotion when control is achieved. (2)
- Reassess diagnosis if no improvement is seen within 2 weeks. Before prescribing for more than 2 weeks, any additional benefits of extending treatment up to 4 weeks should be weighed against the risk of HPA axis suppression and local adverse reactions. (2)
- Avoid use under occlusion or in the diaper area. (2)
- LOCOID Lotion is not for oral, ophthalmic, or intravaginal use. (2)

3 DOSAGE FORMS AND STRENGTHS

Lotion: 0.1% (1 mg/g) (3)

4 CONTRAINDICATIONS

None. (4)

5 WARNINGS AND PRECAUTIONS

- Endocrine System Adverse Reactions:
- Reversible hypothalamic-pituitary-adrenal (HPA) axis suppression may occur, with the potential for glucocorticosteroid insufficiency. Consider periodic evaluations for HPA axis suppression if LOCOID Lotion is applied to large surface areas or used under occlusion. If HPA axis suppression is noted, reduce the application frequency, discontinue use, or switch to a lower potency corticosteroid. (5.1, 8.4)
- Systemic effects of topical corticosteroids may also include manifestations of Cushing’s syndrome, hyperglycemia, and glucosuria. (5.1, 8.4)
- Pediatric patients may be more susceptible to systemic toxicity due to their larger skin-surface-to-body-mass ratios. (5.1, 8.4)
- Ophthalmic Adverse Reactions: Topical corticosteroids, including LOCOID Lotion, may increase the risk of cataracts and glaucoma. If visual symptoms occur, consider referral to an ophthalmologist. (5.2)
- Skin Infections: Initiate appropriate therapy if concomitant skin infections develop. (5.3)

6 ADVERSE REACTIONS

The most common adverse reactions (>1%) are application site reactions. (6)

To report SUSPECTED ADVERSE REACTIONS, contact Bausch Health US, LLC at 1-800-321-4576 and/or FDA at 1-800-FDA-1088 or www.fda.gov/medwatch.

FULL PRESCRIBING INFORMATION

1 INDICATIONS AND USAGE

LOCOID® Lotion is indicated for the topical treatment of mild to moderate atopic dermatitis in patients 3 months of age and older.

2 DOSAGE AND ADMINISTRATION

- Apply LOCOID Lotion for up to 2 weeks as a thin layer to the affected skin two times daily and rub in gently.

Discontinue LOCOID Lotion when control is achieved.

- If no improvement is seen within 2 weeks, consider reassessment of the diagnosis. Before prescribing for more than 2 weeks, the additional benefits of extending treatment up to 4 weeks should be weighed against the risk of endocrine system adverse reactions and local adverse reactions [see Warnings and Precautions (5.1), Adverse Reactions (6.1, 6.2)].
- LOCOID Lotion is not for oral, ophthalmic, or intravaginal use.
- Do not use LOCOID Lotion [see Warnings and Precautions (5.1)]:
- With occlusive dressings unless directed by a healthcare provider. Avoid use in the diaper area, as diapers or plastic pants may constitute occlusive dressings.
- On the face, underarms, or groin areas unless directed by a healthcare provider.

3 DOSAGE FORMS AND STRENGTHS

Lotion: Each gram contains 1 mg of hydrocortisone butyrate (0.1%) in a white to off-white lotion base.

4 CONTRAINDICATIONS

None.

5 WARNINGS AND PRECAUTIONS

5.1 Endocrine System Adverse Reactions

Hypothalamic-Pituitary-Adrenal (HPA) Axis Suppression

Use of topical corticosteroids, including LOCOID Lotion, can cause systemic adverse reactions including reversible hypothalamic-pituitary-adrenal (HPA) axis suppression with the potential for clinical glucocorticosteroid insufficiency. Factors that predispose a patient to HPA axis suppression include the use of high-potency steroids, large treatment surface areas, prolonged use, use of occlusive dressings, altered skin barrier, liver failure, and young age. Such patients should be considered for periodic evaluation of the HPA axis. This may be done by using cosyntropin (ACTH1-24) stimulation testing (CST). If HPA axis suppression is noted, reduce the frequency of application or discontinue LOCOID Lotion, or substitute with a less potent corticosteroid. Signs and symptoms of glucocorticosteroid insufficiency may occur, requiring supplemental systemic corticosteroids [see Adverse Reactions (6)].

Studies conducted in pediatric subjects demonstrated reversible HPA axis suppression after use of LOCOID Lotion. Pediatric patients may be more susceptible than adults to systemic toxicity from equivalent doses of LOCOID Lotion due to their larger skin-surface-to-body-mass ratios [see Use in Specific Populations (8.4)].

Cushing’s Syndrome, Hyperglycemia, and Glucosuria

Systemic adverse reactions of topical corticosteroids, including LOCOID Lotion, may also include manifestations of Cushing’s syndrome, hyperglycemia, and glucosuria.

Additional Considerations for Endocrine Adverse Reactions

Use of more than one corticosteroid-containing product at the same time may increase total systemic corticosteroid exposure.

Minimize systemic corticosteroid adverse reactions by mitigating the risk factors for increased systemic absorption and using LOCOID Lotion as recommended [see Dosage and Administration (2)].

5.2 Ophthalmic Adverse Reactions

Use of topical corticosteroids, including LOCOID Lotion, may increase the risk of posterior subcapsular cataracts and glaucoma. Cataracts and glaucoma have been reported in post-marketing experience with the use of topical corticosteroid products [see Adverse Reactions (6.2)].

Avoid contact of LOCOID Lotion with eyes. Advise patients to report any visual symptoms and consider referral to an ophthalmologist for evaluation.

5.3 Skin Infections

Use of topical corticosteroids, including LOCOID Lotion, may delay healing or worsen concomitant skin infections. If skin infections are present or develop, an appropriate antimicrobial agent should be used. If a favorable response does not occur promptly, use of LOCOID Lotion should be discontinued until the infection has been adequately controlled [see Adverse Reactions (6)].

5.4 Allergic Contact Dermatitis

Use of topical corticosteroids, including LOCOID Lotion, can cause allergic contact dermatitis [see Adverse Reactions (6)]. Allergic contact dermatitis with corticosteroids is usually diagnosed by observing a failure to heal rather than noticing a clinical exacerbation. Such an observation should be corroborated with appropriate patch testing. Discontinue LOCOID Lotion if the diagnosis is established.

6 ADVERSE REACTIONS

The following adverse reactions are discussed in greater detail in other sections of the labeling:

- HPA axis suppression [see Warnings and Precautions (5.1), Use in Specific Populations (8.4)]
- Ophthalmic Adverse Reactions [see Warnings and Precautions (5.2)]
- Skin infections [see Warnings and Precautions (5.3)]
- Allergic contact dermatitis [see Warnings and Precautions (5.4)]

6.1 Clinical Trials Experience

Because clinical trials are conducted under widely varying conditions, adverse reaction rates observed in the clinical trials of a drug cannot be directly compared to rates in the clinical trials of another drug and may not reflect the rates observed in practice.

The safety data described below reflect exposure to LOCOID Lotion applied topically twice daily for up to 4 weeks in vehicle-controlled clinical trials of 284 pediatric subjects 3 months to 18 years of age and 301 adult subjects with mild to moderate atopic dermatitis [see Clinical Studies (14)].

The incidence of selected adverse reactions reported by ≥1% of subjects during the studies is presented in Table 1 and Table 2.

Table 1. Adverse Reactions in ≥1% of LOCOID Lotion-treated Pediatric Subjects 3 Months to 18 Years of Age with Mild to Moderate Atopic Dermatitis
 | LOCOID Lotion; (n=139) n (%) | Vehicle; (n=145) n (%)
Application site reactions, including application site burning, pruritus, dermatitis, erythema, eczema, inflammation, or irritation | 2 (1) | 20 (14)
Infantile acne | 1 (1) | 0 (0)
Skin depigmentation | 1 (1) | 0 (0)

Table 2. Adverse Reactions in ≥1% of LOCOID Lotion-treated Adult Subjects with Mild to Moderate Atopic Dermatitis
 | LOCOID Lotion; (n=151) n (%) | Vehicle; (n=150) n (%)
Application site reactions, including application site burning, dermatitis, eczema, erythema, or pruritus | 5 (3) | 7 (5)

6.2 Postmarketing Experience

The following adverse reactions have been identified during postapproval use of topical corticosteroids, including LOCOID Lotion. Because these reactions are reported voluntarily from a population of uncertain size, it is not always possible to reliably estimate their frequency or establish a causal relationship to drug exposure.

Local Adverse Reactions: folliculitis, acneiform eruptions, perioral dermatitis, allergic contact dermatitis, secondary infection, skin atrophy, striae, miliaria, and telangiectasia.

Ophthalmic Adverse Reactions: blurred vision, cataracts, glaucoma, and increased intraocular pressure.

8 USE IN SPECIFIC POPULATIONS

8.1 Pregnancy

Pregnancy

Risk Summary

There are no controlled or large-scale epidemiologic studies with LOCOID Lotion in pregnant women, and available data on hydrocortisone butyrate use in pregnant women have not identified a drug associated risk for major birth defects, miscarriages, or adverse maternal or fetal outcomes.

In animal reproduction studies, when administered subcutaneously or topically to pregnant rats, rabbits, and mice, hydrocortisone butyrate induced adverse reproductive and developmental outcomes, including abortion, fetal death, malformation, delayed ossification, decrease in fetal weight, and delay in sexual maturation (see Data). The available data do not allow the calculation of relevant comparisons between the systemic exposure of hydrocortisone butyrate observed in animal studies and the systemic exposure that would be expected in humans after topical use of LOCOID Lotion.

The background risk of major birth defects and miscarriage for the indicated population is unknown. All pregnancies have a background risk of birth defect, loss, or other adverse outcomes. In the U.S. general population, the estimated background risk of major birth defects and miscarriage in clinically recognized pregnancies is 2-4% and 15-20%, respectively.

Data

Animal Data

Systemic embryofetal development studies were conducted in rats and rabbits. Subcutaneous doses of 0.6, 1.8, and 5.4 mg/kg/day hydrocortisone butyrate were administered to pregnant female rats during gestation days 6 – 17. In the presence of maternal toxicity, fetal effects noted at 5.4 mg/kg/day included increased ossification variations and unossified sternebra. No treatment-related embryofetal toxicity or malformation were noted at 5.4 and 1.8 mg/kg/day, respectively.

Subcutaneous doses of 0.1, 0.2 and 0.3 mg/kg/day hydrocortisone butyrate were administered to pregnant female rabbits during gestation days 7 – 20. Increased abortion was noted at 0.3 mg/kg/day. In the absence of maternal toxicity, a dose-dependent decrease in fetal body weight was noted at doses ≥0.1 mg/kg/day. Embryofetal toxicities (reduction in litter size, decreased number of viable fetuses, and increased post-implantation loss) were noted at doses ≥0.2 mg/kg/day. Additional fetal effects included delayed ossification noted at doses ≥0.1 mg/kg/day and increased fetal malformations (primarily skeletal malformations) noted at doses ≥0.2 mg/kg/day. A dose at which no embryofetal toxicity or malformation was observed was not established in this study.

Additional systemic embryofetal development studies were conducted in rats and mice. Subcutaneous doses of 0.1 and 9 mg/kg/day hydrocortisone butyrate were administered to pregnant female rats during gestation days 9 – 15. In the presence of maternal toxicity, an increase in fetal death and fetal resorption and an increase in ossification of caudal vertebrae were noted at 9 mg/kg/day. No treatment-related embryofetal toxicity or malformation was noted at 0.1 mg/kg/day.

Subcutaneous doses of 0.2 and 1 mg/kg/day hydrocortisone butyrate were administered to pregnant female mice during gestation days 7 – 13. In the absence of maternal toxicity, an increased number of cervical ribs and one fetus with clubbed legs were noted at 1 mg/kg/day. No treatment-related embryofetal toxicity or malformation was noted at 1 and 0.2 mg/kg/day.

No topical embryofetal development studies were conducted with hydrocortisone butyrate lotion. However, topical embryofetal development studies were conducted in rats and rabbits with a hydrocortisone butyrate ointment formulation. Topical doses of 1% and 10% hydrocortisone butyrate ointment were administered to pregnant female rats during gestation days 6 – 15 or pregnant female rabbits during gestation days 6 – 18. A dose-dependent increase in fetal resorption was noted in rabbits and fetal resorptions were noted in rats at the 10% hydrocortisone butyrate ointment dose. No treatment-related embryofetal toxicity was noted at the 1% hydrocortisone butyrate ointment dose in rats. A dose at which no embryofetal toxicity was observed in rabbits after topical administration of hydrocortisone butyrate ointment was not established. No treatment-related malformation was noted at a dose of 10% hydrocortisone butyrate ointment in rats or rabbits.

A peri- and post-natal development study was conducted in rats. Subcutaneous doses of 0.6, 1.8 and 5.4 mg/kg/day hydrocortisone butyrate were administered to pregnant female rats from gestation day 6 to lactation day 20. In the presence of maternal toxicity, a dose-dependent decrease in fetal weight was noted at doses ≥1.8 mg/kg/day. No treatment-related fetal toxicity was noted at 0.6 mg/kg/day. A delay in sexual maturation was noted at 5.4 mg/kg/day. No treatment-related effects on sexual maturation were noted at 1.8 mg/kg/day. No treatment-related effects on behavioral development or subsequent reproductive performance were noted at 5.4 mg/kg/day.

8.2 Lactation

Risk Summary

There are no data on the presence of hydrocortisone butyrate in human or animal milk, effects on the breastfed infant, or effects on milk production.

Systemically administered corticosteroids appear in human milk and could suppress growth, interfere with endogenous corticosteroid production, or cause other untoward effects. It is not known whether topical administration of LOCOID Lotion could result in sufficient systemic absorption to produce detectable quantities in human milk.

The developmental and health benefits of breastfeeding should be considered along with the mother’s clinical need for LOCOID Lotion and any potential adverse effects on the breastfed infant from LOCOID Lotion or from the underlying maternal condition.

Clinical Considerations

To minimize potential exposure to the breastfed infant via breast milk, use LOCOID Lotion on the smallest area of skin and for the shortest duration possible while breastfeeding. Advise breastfeeding women to wash off prior to breastfeeding any LOCOID Lotion that has been applied to the areas at risk for direct infant contact.

8.4 Pediatric Use

The safety and effectiveness of LOCOID Lotion for the topical treatment of mild to moderate atopic dermatitis have been established in pediatric patients 3 months of age and older. Use of LOCOID Lotion for this indication is supported by evidence from an adequate and well-controlled trial in 284 pediatric patients 3 months to 18 years of age with mild to moderate atopic dermatitis.

The safety and effectiveness of LOCOID Lotion have not been established in pediatric patients younger than 3 months of age.

Endocrine Adverse Reactions

Eighty-four (84) pediatric subjects (3 months to less than 18 years of age) with moderate to severe atopic dermatitis affecting at least 25% of body surface area (BSA) treated with LOCOID Lotion three times daily for up to 4 weeks were assessed for HPA axis suppression. The disease severity (moderate to severe atopic dermatitis) and the dosing regimen (three times daily) in this HPA axis trial were different from the subject population (mild to moderate atopic dermatitis) and the dosing regimen (twice daily) for which LOCOID Lotion is indicated. Seven of the 82 evaluable subjects (8.5%) demonstrated laboratory evidence of HPA axis suppression, where the criterion for defining HPA axis suppression was a serum cortisol level of less than or equal to 18 mcg/dL after cosyntropin stimulation. Subjects with HPA axis suppression ranged from 1 to 12 years of age and, at the time of enrollment, had 35% to 90% BSA involvement. These subjects did not develop any other signs or symptoms of HPA axis suppression. At the first follow-up visit, approximately 1 month after the conclusion of treatment, cosyntropin stimulation results of all subjects had returned to normal, with the exception of one subject. This last subject recovered adrenal function by the second post-treatment visit, 55 days post-treatment [see Clinical Pharmacology (12.2)].

Because of higher skin-surface-to-body-mass ratios, pediatric patients are at a greater risk than adults of HPA axis suppression when they are treated with topical corticosteroids [see Warnings and Precautions (5.1)]. They are therefore also at a greater risk of glucocorticosteroid insufficiency after withdrawal of treatment and of Cushing’s syndrome while on treatment.

Cushing’s syndrome, linear growth retardation, delayed weight gain, and intracranial hypertension have been reported in pediatric patients receiving topical corticosteroids. Manifestations of adrenal suppression in pediatric patients include low plasma cortisol levels to an absence of response to ACTH stimulation. Manifestations of intracranial hypertension include bulging fontanelles, headaches, and bilateral papilledema.

8.5 Geriatric Use

Clinical trials of LOCOID Lotion did not include sufficient numbers of subjects aged 65 years and over to determine whether they respond differently from younger adult subjects.

11 DESCRIPTION

LOCOID (hydrocortisone butyrate) Lotion, 0.1% contains hydrocortisone butyrate, a non-fluorinated hydrocortisone ester, for topical use.

Hydrocortisone butyrate is a corticosteroid.

The chemical name of hydrocortisone butyrate is Pregn-4-ene-3,20-dione, 11,21-dihydroxy-17-[(1-oxobutyl)oxy(11β)-]. It has the following structural formula:

Hydrocortisone butyrate is a white to off-white powder with a molecular weight of 432.56, and a molecular formula of C25H36O6. It is practically insoluble in water, slightly soluble in ether, soluble in methanol, alcohol, and acetone, and freely soluble in chloroform.

Each gram of LOCOID Lotion contains 1 mg of hydrocortisone butyrate in a white to off-white lotion base consisting of anhydrous citric acid, ceteth-20, cetostearyl alcohol, butylated hydroxytoluene (BHT), butylparaben, light mineral oil, propylparaben, purified water, safflower oil, sodium citrate, and white petrolatum.

12 CLINICAL PHARMACOLOGY

12.1 Mechanism of Action

Corticosteroids play a role in cellular signaling, immune function, inflammation, and protein regulation; however, the precise mechanism of action in atopic dermatitis is unknown.

12.2 Pharmacodynamics

Pharmacodynamics of LOCOID Lotion is unknown.

Hypothalamic-Pituitary-Adrenal (HPA) Axis Suppression

Eighty-four (84) pediatric subjects (3 months to less than 18 years of age) with moderate to severe atopic dermatitis affecting at least 25% of body surface area (BSA) treated with LOCOID Lotion three times daily for up to 4 weeks were assessed for HPA axis suppression. The disease severity (moderate to severe atopic dermatitis) and the dosing regimen (three times daily) in this HPA axis trial were different from the subject population (mild to moderate atopic dermatitis) and the dosing regimen (twice daily) for which LOCOID Lotion is indicated. Seven of the 82 evaluable subjects (8.5%) demonstrated laboratory evidence of HPA axis suppression, where the criterion for defining HPA axis suppression was a serum cortisol level of less than or equal to 18 mcg/dL after cosyntropin stimulation. Subjects with HPA axis suppression ranged from 1 to 12 years of age and, at the time of enrollment, had 35% to 90% BSA involvement. These subjects did not develop any other signs or symptoms of HPA axis suppression. At the first follow-up visit, approximately 1 month after the conclusion of treatment, cosyntropin stimulation results of all subjects had returned to normal, with the exception of one subject. This last subject recovered adrenal function by the second post-treatment visit, 55 days post-treatment [see Warnings and Precautions (5.1), Use in Specific Populations (8.4)].

12.3 Pharmacokinetics

No studies were conducted to determine the pharmacokinetics of LOCOID Lotion.

The extent of percutaneous absorption of topical corticosteroids is determined by many factors, including the vehicle, the integrity of the epidermal barrier, and the use of occlusive dressings.

Topical corticosteroids can be absorbed through normal intact skin. Inflammation and/or other disease processes in the skin, occlusive dressings, or widespread application may increase percutaneous absorption.

Once absorbed through the skin, topical corticosteroids are handled through pharmacokinetic pathways similar to systemically administered corticosteroids.

13 NONCLINICAL TOXICOLOGY

13.1 Carcinogenesis, Mutagenesis, Impairment of Fertility

In a 2-year dermal rat carcinogenicity study with LOCOID Lotion, hydrocortisone butyrate was administered to Sprague-Dawley rats at topical doses of 0.05, 0.15, and 0.3 mg/kg/day in males and 0.1, 0.25, and 0.5 mg/kg/day in females (0.1% lotion). No drug-related tumors were noted in this study up to the highest doses evaluated in this study of 0.3 mg/kg/day in males and 0.5 mg/kg/day in females.

Hydrocortisone butyrate revealed no evidence of mutagenic or clastogenic potential based on the results of two in vitro genotoxicity tests (Ames test and L5178Y/TK+/- mouse lymphoma assay) and one in vivo genotoxicity test (mouse micronucleus assay).

No evidence of impairment of fertility or effect on mating performance was observed in a fertility and general reproductive performance study conducted in male and female rats at subcutaneous doses up to 1.8 mg/kg/day. Mild effects on maternal animals, such as reduced food consumption and a subsequent reduction in body weight gain, were seen at doses ≥0.6 mg/kg/day.

14 CLINICAL STUDIES

In a multicenter, randomized, vehicle-controlled trial of 284 pediatric subjects 3 months to 18 years of age with mild to moderate atopic dermatitis, LOCOID Lotion or vehicle was applied topically twice daily for up to 4 weeks. Treatment success was assessed at day 29 (after 28 days of treatment) and was defined as the proportion of subjects who achieved both “clear” or “almost clear” and at least a 2-grade improvement from baseline on a 5-point Physician’s Global Assessment (PGA) scale. The trial results are shown in Table 3.

Table 3. Efficacy Results at Day 29 in Pediatric Subjects 3 Months to 18 Years of Age with Mild to Moderate Atopic Dermatitis
 | LOCOID Lotion; (n=139) | Vehicle; (n=145)
Number (%) successes | 68 (49%) | 35 (24%)

16 HOW SUPPLIED/STORAGE AND HANDLING

How Supplied

LOCOID Lotion, 0.1% is white to off-white in color and supplied in:

- 2 fl. oz. bottle: NDC 16781-392-02
- 4 fl. oz. bottle: NDC 16781-392-04

Storage and Handling

Store at 25°C (77°F); excursions permitted to 15° to 30°C (59° to 86°F) [see USP Controlled Room Temperature]. Protect from freezing.

17 PATIENT COUNSELING INFORMATION

Patients using LOCOID Lotion should receive the following information and instructions:

Administration Instructions

Instruct patients to apply a thin layer to the affected skin two times daily and rub in gently [see Dosage and Administration (2)].

Advise patients to discontinue LOCOID Lotion when control is achieved [see Dosage and Administration (2)].

Advise patients to avoid use for longer than 2 weeks. Instruct patients to contact their healthcare provider if no improvement is seen within 2 weeks [see Dosage and Administration (2)].

Advise patients to NOT [see Dosage and Administration (2) and Warnings and Precautions (5.1)]:

- Bandage, otherwise cover, or wrap the affected skin area unless directed by their healthcare provider.
- Use LOCOID Lotion in the diaper area, as diapers or plastic pants may constitute occlusive dressings.
- Use LOCOID Lotion on the face, underarms, or groin areas unless directed by their healthcare provider.

Endocrine System Adverse Reactions

Instruct patients not to use other corticosteroid-containing products while using LOCOID Lotion without first consulting their healthcare provider [see Warnings and Precautions (5.1)].

Ophthalmic Adverse Reactions

Advise patients to avoid contact with the eyes. Instruct patients to report any visual symptoms to their healthcare providers [see Warnings and Precautions (5.4)].

Lactation

Advise breastfeeding women to use LOCOID Lotion on the smallest area of skin and for the shortest duration possible while breastfeeding. Advise to wash off prior to breastfeeding any LOCOID Lotion that has been applied to the areas at risk for direct infant contact. [see Use in Specific Populations (8.2)].

Distributed by:

Bausch Health US, LLC
Bridgewater, NJ 08807 USA

Manufactured by:

Ferndale Laboratories, Inc.
Ferndale, MI 48220 USA

U.S. Patent Number: 7,981,877

Locoid is a trademark of Leo Pharma A/S used under license.
© 2023 Bausch Health Companies Inc. or its affiliates

9421803

PACKAGE LABEL

PRINCIPAL DISPLAY PANEL – Locoid Lotion 4 fl. oz. Carton

NDC 16781-392-04

Locoid®
(hydrocortisone butyrate)
Lotion, 0.1%

For topical use only
Not for eye use

Rx only
4 fl. oz. (118 mL)

Ortho Dermatologics